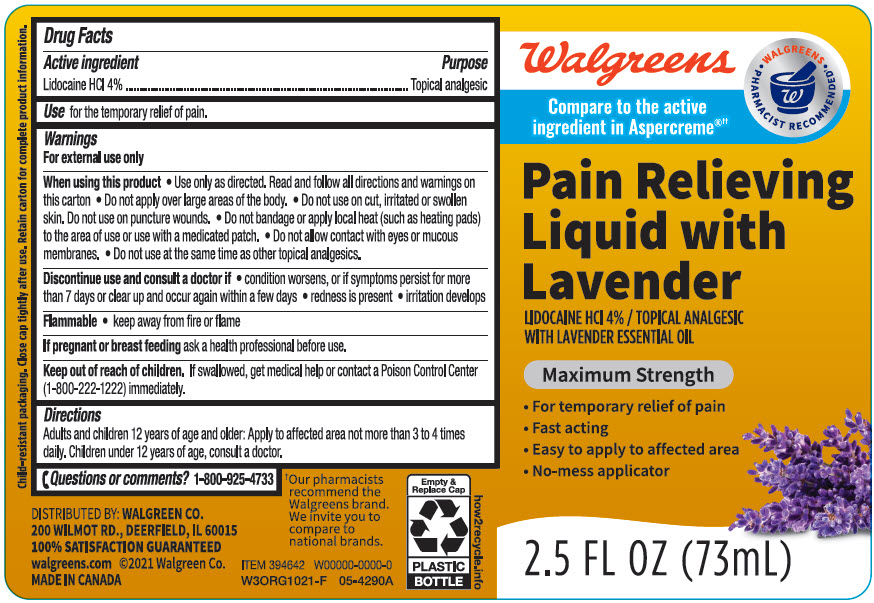 DRUG LABEL: Walgreens Pain Relieving with Lavender
NDC: 0363-1225 | Form: LIQUID
Manufacturer: Walgreen Company
Category: otc | Type: HUMAN OTC DRUG LABEL
Date: 20241031

ACTIVE INGREDIENTS: LIDOCAINE HYDROCHLORIDE 40 mg/1 mL
INACTIVE INGREDIENTS: ALCOHOL; ALOE VERA LEAF; AMINOMETHYLPROPANOL; C30-45 ALKYL CETEARYL DIMETHICONE CROSSPOLYMER; CAPRYLYL TRISILOXANE; CETOSTEARYL ALCOHOL; CETETH-20 PHOSPHATE; DIHEXADECYL PHOSPHATE; DIMETHICONE; EDETATE DISODIUM; ETHYLHEXYLGLYCERIN; GLYCERYL MONOSTEARATE; ISOHEXADECANE; LAVENDER OIL; PHENOXYETHANOL; POLYSORBATE 60; STEARETH-21; WATER

Walgreens Pain Relieving Liquid with Lavender
Topical Analgesic

Drug Facts

Active ingredient

Lidocaine HCl 4%

Purpose

Topical analgesic

INDICATIONS AND USAGE

Use for the temporary relief of pain.

Warnings

For external use only

When using this product

- Use only as directed. Read and follow all directions and warnings on this carton
- Do not apply over large areas of the body.
- Do not use on cut, irritated or swollen skin. Do not use on puncture wounds.
- Do not bandage or apply local heat (such as heating pads) to the area of use or use with a medicated patch.
- Do not allow contact with eyes or mucous membranes.
- Do not use at the same time as other topical analgesics.

Discontinue use and consult a doctor if

- condition worsens, or if symptoms persist for more than 7 days or clear up and occur again within a few days
- redness is present
- irritation develops

Flammable

- keep away from fire or flame

PREGNANCY OR BREAST FEEDING

If pregnant or breast feeding ask a health professional before use.

Keep out of reach of children. If swallowed, get medical help or contact a Poison Control Center (1-800-222-1222) immediately.

Directions

Adults and children 12 years of age and older: Apply to affected area not more than 3 to 4 times daily. Children under 12 years of age, consult a doctor.

Other information store at room temperature.

Inactive ingredients

acrylates/C10-30 alkyl acrylate crosspolymer, alcohol denat., aloe barbadensis leaf juice, aminomethyl propanol, C30-45 alkyl cetearyl dimethicone crosspolymer, caprylyl methicone, cetearyl alcohol, ceteth-20 phosphate, dicetyl phosphate, dimethicone, disodium EDTA, ethylhexylglycerin, fragrance, glyceryl stearate, isohexadecane, lavandula angustifolia (lavender) oil, phenoxyethanol, polysorbate 60, steareth-21, water.

Questions or comments?

1-800-925-4733

DISTRIBUTED BY: WALGREEN CO.
200 WILMOT RD., DEERFIELD, IL 60015

PRINCIPAL DISPLAY PANEL - 73 mL Bottle Label

Walgreens

Compare to the active
ingredient in Aspercreme®††

WALGREENS
• PHARMACIST RECOMMENDED†•

Pain Relieving
Liquid with
Lavender

LIDOCAINE HCl 4% / TOPICAL ANALGESIC
WITH LAVENDER ESSENTIAL OIL

Maximum Strength

- For temporary relief of pain
- Fast acting
- Easy to apply to affected area
- No-mess applicator

2.5 FL OZ (73mL)

Lavender
Essential Oil